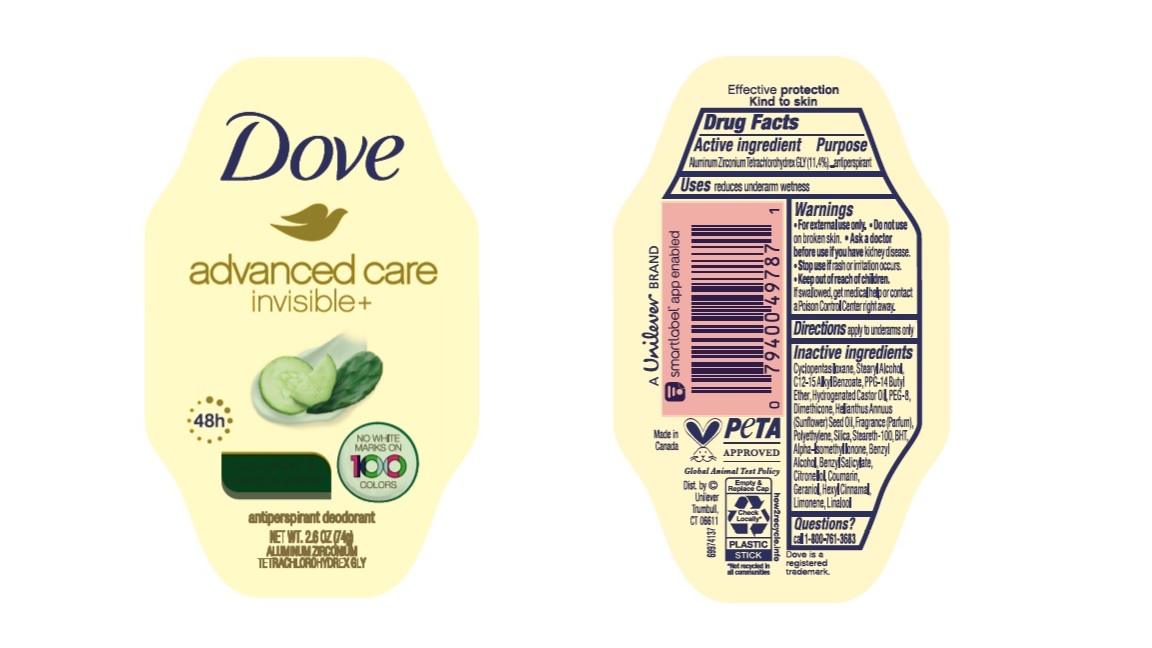 DRUG LABEL: Dove
NDC: 64942-2132 | Form: STICK
Manufacturer: Conopco Inc. d/b/a/ Unilever
Category: otc | Type: HUMAN OTC DRUG LABEL
Date: 20241024

ACTIVE INGREDIENTS: ALUMINUM ZIRCONIUM TETRACHLOROHYDREX GLY 11.4 g/100 g
INACTIVE INGREDIENTS: .BETA.-CITRONELLOL, (R)-; .ALPHA.-HEXYLCINNAMALDEHYDE; LIMONENE, (+)-; HIGH DENSITY POLYETHYLENE; CYCLOMETHICONE 5; HYDROGENATED CASTOR OIL; BUTYLATED HYDROXYTOLUENE; PPG-14 BUTYL ETHER; STEARYL ALCOHOL; SUNFLOWER OIL; SILICON DIOXIDE; ALKYL (C12-15) BENZOATE; DIMETHICONE; STEARETH-100; POLYETHYLENE GLYCOL 400; ISOPROPYL PALMITATE; BENZYL SALICYLATE; BENZYL ALCOHOL; COUMARIN; ISOMETHYL-.ALPHA.-IONONE; LINALOOL, (+/-)-; GERANIOL

Dove Advanced Care Invisible+ Cucumber & Cactus Water Antiperspirant Deodorant

Drug Facts

Active ingredient

Aluminum Zirconium Tetrachlorohydrex GLY (11.4 %)

Purpose

antiperspirant

Uses

reduces underarm wetness

• Keep out of reach of children.

If swallowed, get medical help or contact a Poison Control Center right away.

Directions

apply to underarms only

Inactive ingredients

Cyclopentasiloxane, Stearyl Alcohol, C12-15 Alkyl Benzoate, PPG-14 Butyl Ether, Hydrogenated Castor Oil, PEG-8, Dimethicone, Helianthus Annuus (Sunflower) Seed Oil, Fragrance (Parfum), Polyethylene, Silica, Steareth-100, BHT, Alpha-Isomethyl Ionone, Benzyl Alcohol, Benzyl Salicylate, Citronellol, Coumarin, Geraniol, Hexyl Cinnamal, Limonene, Linalool

Questions?

Call 1-800-761-3683